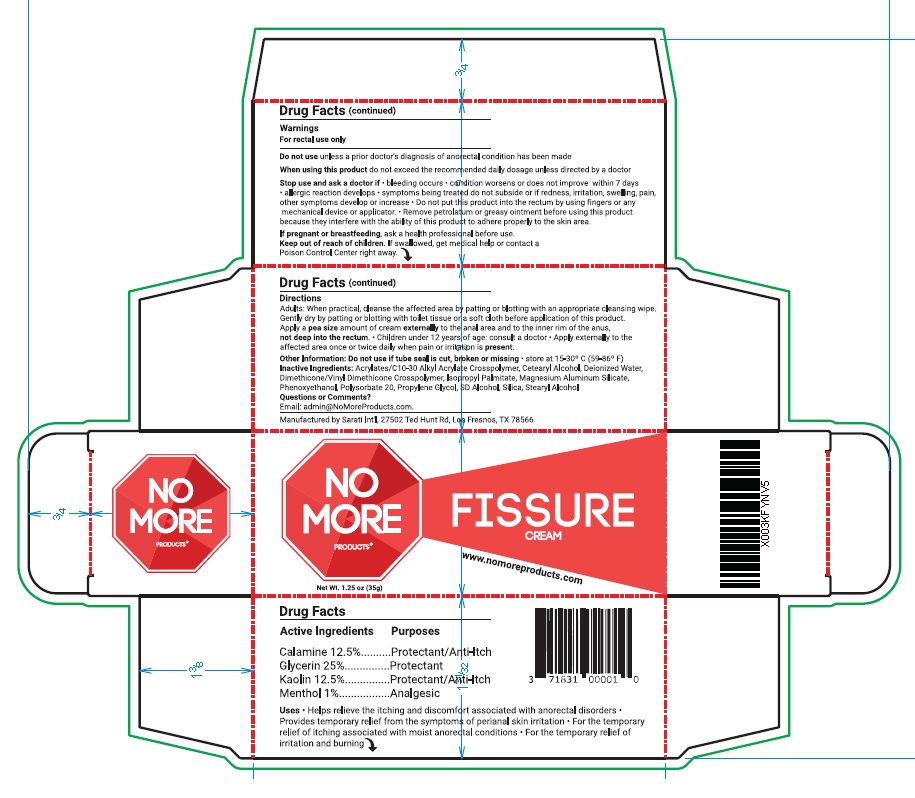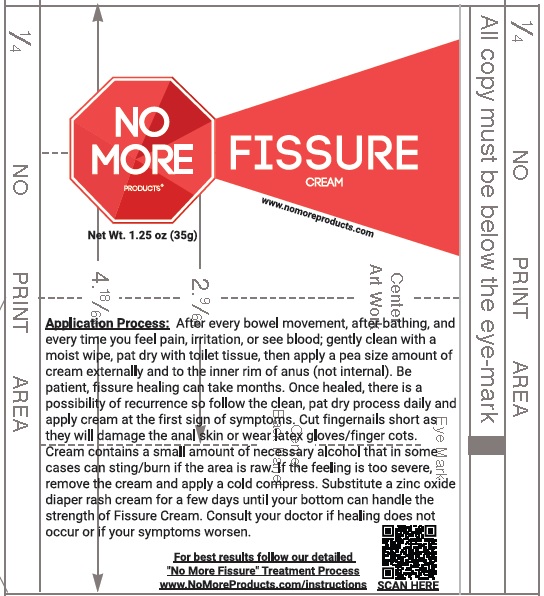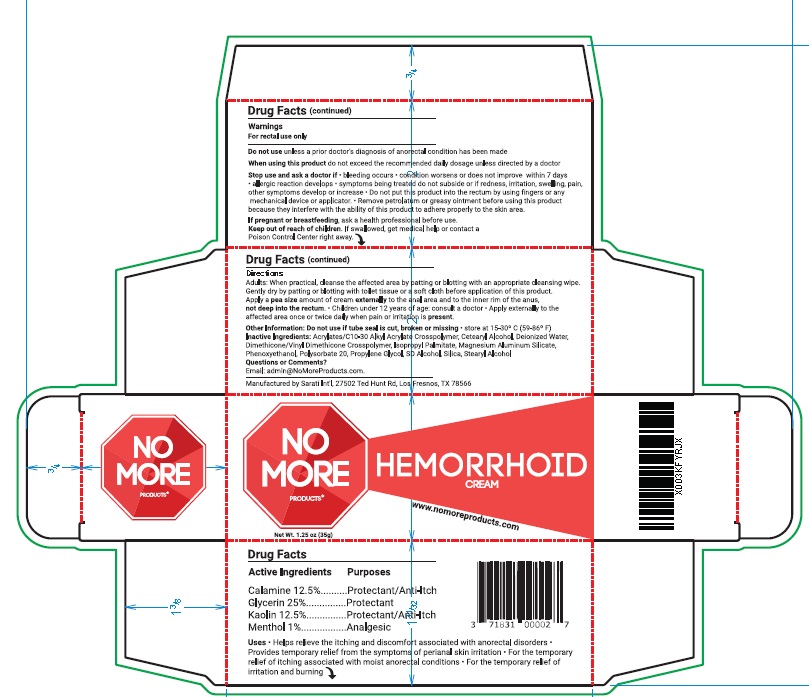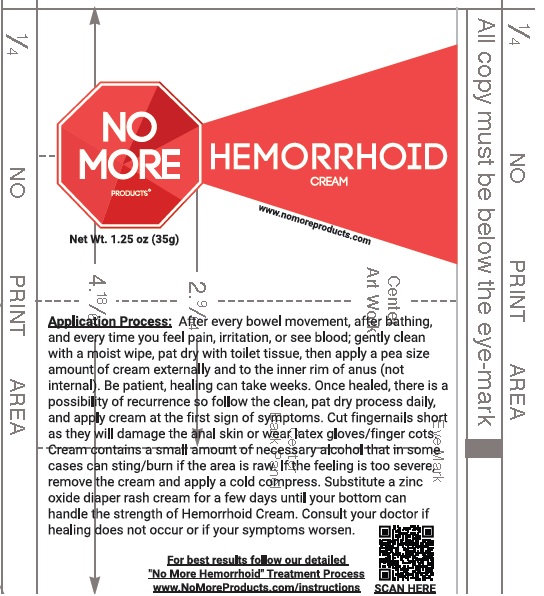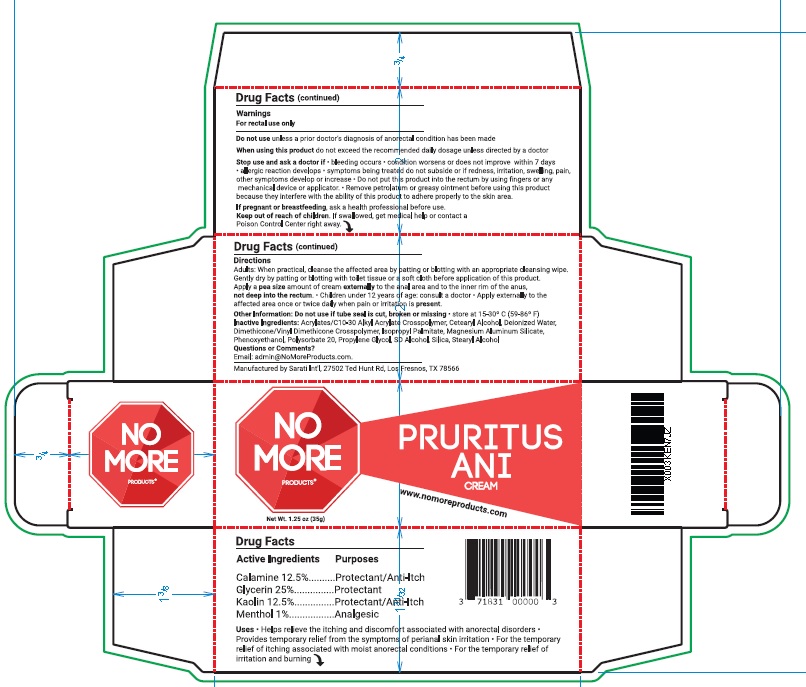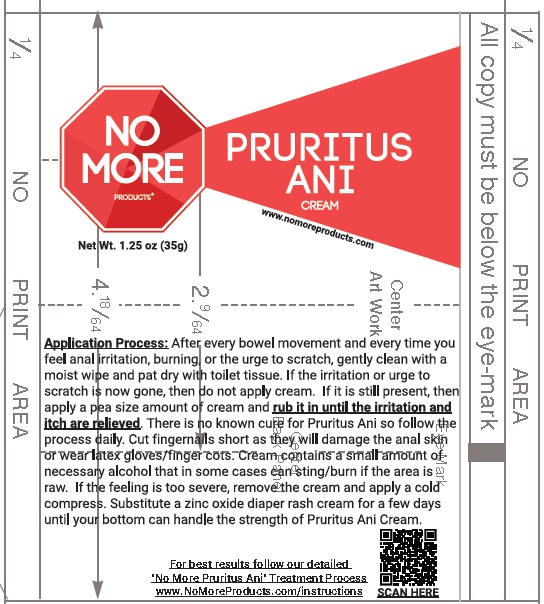 DRUG LABEL: No More Products
NDC: 67676-008 | Form: CREAM
Manufacturer: Sarati International, Inc
Category: otc | Type: HUMAN OTC DRUG LABEL
Date: 20240126

ACTIVE INGREDIENTS: GLYCERIN 25 g/100 g; KAOLIN 12.5 g/100 g; ZINC OXIDE 12.5 g/100 g; MENTHOL 1 g/100 g
INACTIVE INGREDIENTS: CARBOMER INTERPOLYMER TYPE A (ALLYL SUCROSE CROSSLINKED); CETOSTEARYL ALCOHOL; WATER; DIMETHICONE/VINYL DIMETHICONE CROSSPOLYMER (SOFT PARTICLE); ISOPROPYL PALMITATE; MAGNESIUM ALUMINUM SILICATE; PHENOXYETHANOL; POLYSORBATE 20; PROPYLENE GLYCOL; ALCOHOL; SILICON DIOXIDE; STEARYL ALCOHOL

No More Products

Drug Facts

Active Ingredients

Glycerin 25%
Kaolin 12.5%
Calamine 12.5%
Menthol 1%

Purposes

Glycerin ....................................................Protectant
Kaolin .........................................Protectant/Anti-Itch
Calamine ....................................Protectant/Anti-Itch
Menthol .....................................................Analgesic

INDICATIONS AND USAGE

Uses• Helps relieve the itching and discomfort associated with anorectal disorders •
Provides temporary relief from the symptoms of perianal skin irritation • For the temporary
relief of itching associated with moist anorectal conditions • For the temporary relief of
irritation and burning

Warnings
For rectal use only
Do not useunless a prior doctor’s diagnosis of anorectal condition has been made
When using this productdo not exceed the recommended daily dosage unless directed by a doctor
Stop use and ask a doctor if• bleeding occurs • condition worsens or does not improve within 7 days
• allergic reaction develops • symptoms being treated do not subside or if redness, irritation, swelling, pain,
other symptoms develop or increase • Do not put this product into the rectum by using fingers or any
mechanical device or applicator. • Remove petrolatum or greasy ointment before using this product
because they interfere with the ability of this product to adhere properly to the skin area.
If pregnant or breastfeeding, ask a health professional before use

Keep out of reach of children.If swallowed, get medical help or contact a Poison
Control Center right away

Directions
Adults: When practical, cleanse the affected area by patting or blotting with an appropriate cleansing wipe.
Gently dry by patting or blotting with toilet tissue or a soft cloth before application of this product.
Apply a pea sizeamount of cream externallyto the anal area and to the inner rim of the anus,
not deep into the rectum. • Children under 12 years of age: consult a doctor • Apply externally to the
affected area once or twice daily when pain or irritation is present.

Other Information:Do not use if tube seal is cut, broken or missing. • store at 15-30º C (59-86º F)

INACTIVE INGREDIENT

Inactive Ingredients:Acrylates/C10-30 Alkyl Acrylate Crosspolymer, Cetearyl Alcohol, Deionized Water,
Dimethicone/Vinyl Dimethicone Crosspolymer, Isopropyl Palmitate, Magnesium Aluminum Silicate,
Phenoxyethanol, Polysorbate 20, Propylene Glycol, SD Alcohol, Silica, Stearyl Alcohol

Questions or Comments?Email: Admin@NoMoreProducts.com

No More Product Labeling

No More Products

Net Wt. 1.25oz (35g)

Manufactured by Sarati Intn'i, 27502 Ted Hunt Rd., Los Fresnos TX 78566

www.nomoreproducts.com

No More Fissure Box

No More Fissure Tube

No More Hemorrhoids Box

No More Hemorrhoids Tube

No More Pruritus Box

No More Pruritus Tube

RES